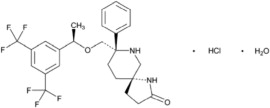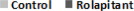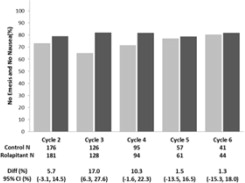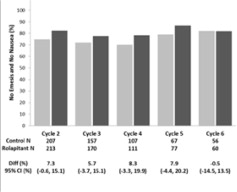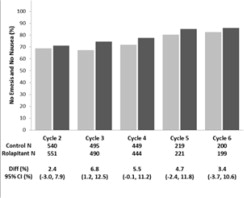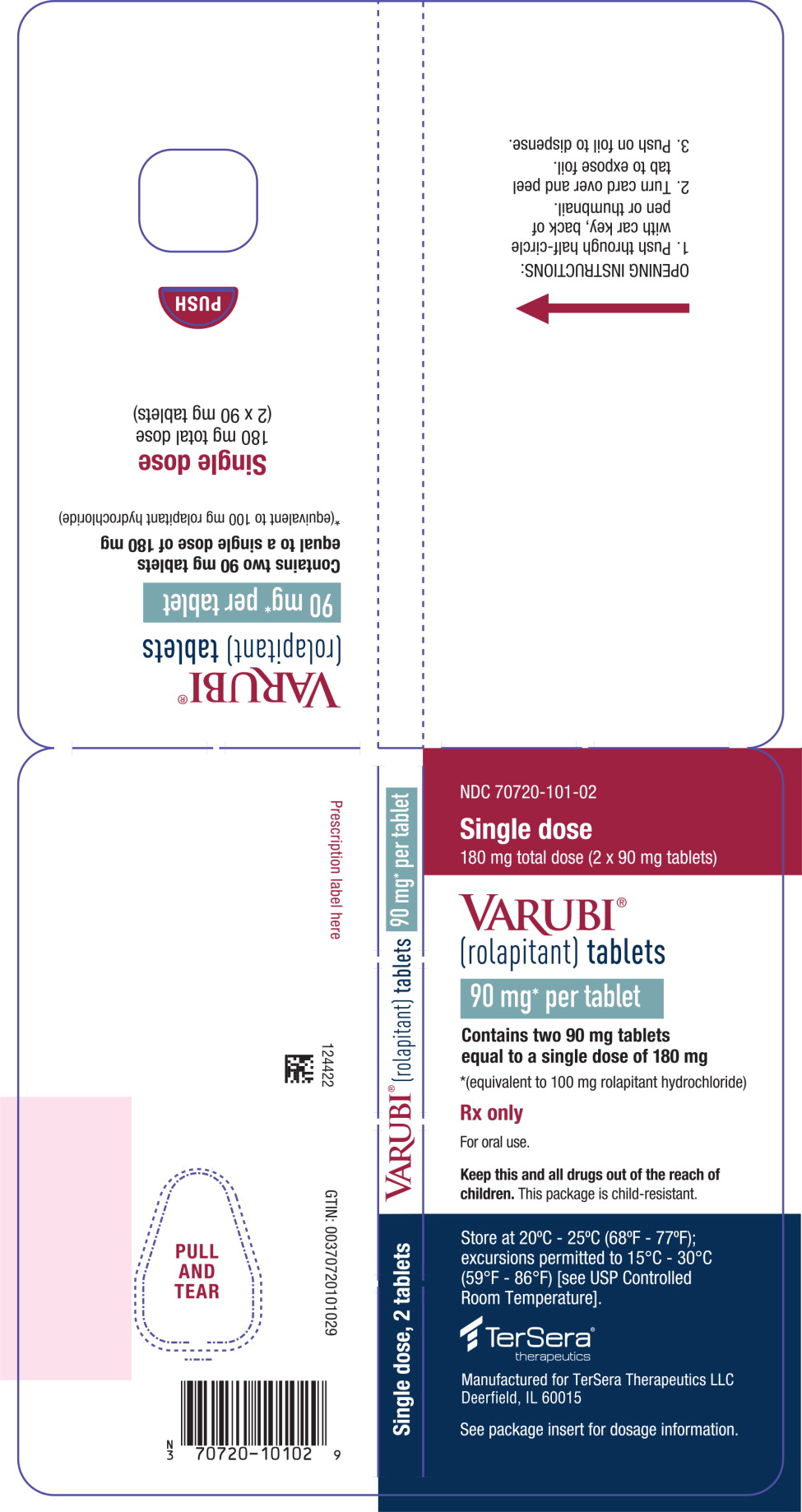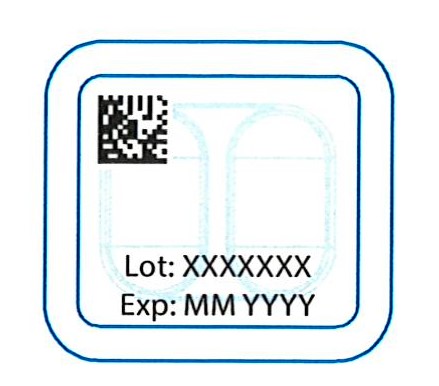 DRUG LABEL: Varubi
NDC: 70720-101 | Form: TABLET
Manufacturer: TerSera Therapeutics LLC
Category: prescription | Type: HUMAN PRESCRIPTION DRUG LABEL
Date: 20200819

ACTIVE INGREDIENTS: ROLAPITANT HYDROCHLORIDE 90 mg/1 1
INACTIVE INGREDIENTS: lactose monohydrate; starch, corn; microcrystalline cellulose; povidone, unspecified; croscarmellose sodium; silicon dioxide; magnesium stearate; polyvinyl alcohol, unspecified; titanium dioxide; polyethylene glycol, unspecified; talc; FD&C Blue NO. 2; polysorbate 80

HIGHLIGHTS OF PRESCRIBING INFORMATION

These highlights do not include all the information needed to use VARUBI safely and effectively. See full prescribing information for VARUBI.
VARUBI® (rolapitant) tablets, for oral use
Initial U.S. Approval: 2015

RECENT MAJOR CHANGES

Dosage and Administration (2) | 8/2020
Contraindications (4) | 8/2020

1 INDICATIONS AND USAGE

VARUBI is a substance P/neurokinin 1 (NK1) receptor antagonist indicated in combination with other antiemetic agents in adults for the prevention of delayed nausea and vomiting associated with initial and repeat courses of emetogenic cancer chemotherapy, including, but not limited to, highly emetogenic chemotherapy. (1)

2 DOSAGE AND ADMINISTRATION

- Administer in combination with dexamethasone and a 5-HT3 receptor antagonist; see full prescribing information for dosing information. (2)
- No dosage adjustment for dexamethasone is required. (2)
- The recommended dosage of VARUBI is 180 mg as a single dose orally within 2 hours prior to the initiation of chemotherapy on Day 1. (2)
- Administer VARUBI prior to the initiation of each chemotherapy cycle, but at no less than 2 week intervals. (2)
- Administer VARUBI without regards to meals. (2)

3 DOSAGE FORMS AND STRENGTHS

Tablets: 90 mg of rolapitant (3)

4 CONTRAINDICATIONS

- CYP2D6 substrates with a narrow therapeutic index (e.g., thioridazine and pimozide) (4, 5.1, 7)
- Pediatric patients less than 2 years of age because of irreversible impairment of sexual development and fertility in juvenile rats (4, 8.4)

5 WARNINGS AND PRECAUTIONS

CYP2D6 Substrates: Rolapitant is a moderate inhibitor of CYP2D6 and significantly increases the plasma concentrations of CYP2D6 substrates for at least 28 days following single dose administration of VARUBI. Before starting VARUBI, consider if patients require:

- thioridazine or pimozide; if so, use an alternative antiemetic to VARUBI or an alternative to thioridazine or pimozide that is not metabolized by CYP2D6.
- other CYP2D6 substrates; if so, consult the prescribing information for the CYP2D6 substrate for additional information about interactions with CYP2D6 inhibitors. (4, 5.1, 7)

6 ADVERSE REACTIONS

Most common adverse reactions (≥3%) are:

- Cisplatin Based Highly Emetogenic Chemotherapy: neutropenia, hiccups and abdominal pain. (6.1)
- Moderately Emetogenic Chemotherapy and Combinations of
  Anthracycline and Cyclophosphamide: decreased appetite, neutropenia, dizziness, dyspepsia, urinary tract infection, stomatitis and anemia. (6.1)

To report SUSPECTED ADVERSE REACTIONS, contact TerSera Therapeutics at 1-844-334-4035 or FDA at 1-800-FDA-1088 or www.fda.gov/medwatch.

7 DRUG INTERACTIONS

- Strong CYP3A4 Inducers (e.g., rifampin): significantly reduced plasma concentrations of rolapitant can decrease the efficacy of VARUBI; avoid use of VARUBI in patients who require chronic administration of such drugs. (7)
- BCRP and P-gp Substrates with a Narrow Therapeutic Index: Oral VARUBI is an inhibitor of BCRP and P-gp and can increase plasma concentrations of the concomitant drug and potential for adverse reactions. See full prescribing information for specific examples. (7)
- Warfarin: Monitor for increased INR or prothrombin time; adjust the dose of warfarin as needed. (7)

FULL PRESCRIBING INFORMATION

1 INDICATIONS AND USAGE

VARUBI® is indicated in combination with other antiemetic agents in adults for the prevention of delayed nausea and vomiting associated with initial and repeat courses of emetogenic cancer chemotherapy, including, but not limited to, highly emetogenic chemotherapy.

2 DOSAGE AND ADMINISTRATION

The recommended dosage of VARUBI in adults in combination with a 5-HT3 receptor antagonist and dexamethasone for the prevention of nausea and vomiting with emetogenic cancer chemotherapy is shown in Table 1. There is no drug interaction between rolapitant and dexamethasone, so no dosage adjustment for dexamethasone is required. Administer a dexamethasone dose of 20 mg on Day 1 [see Clinical Pharmacology (12.3)].

Administer VARUBI prior to the initiation of each chemotherapy cycle, but at no less than 2 week intervals.

Administer VARUBI without regards to meals.

Table 1: Recommended Dosing Regimen of VARUBI
 | Day 1 | Day 2 | Day 3 | Day 4
Prevention of Nausea and Vomiting Associated with Cisplatin-Based Highly Emetogenic Cancer Chemotherapy
VARUBI | 180 mg as a single dose orally within 2 hours prior to initiation of chemotherapy | None
Dexamethasone | 20 mg; 30 min prior to initiation of chemotherapy | 8 mg twice daily | 8 mg twice daily | 8 mg twice daily
5-HT3 receptor antagonist | See the prescribing information for the co-administered 5-HT3 receptor antagonist for appropriate dosing information. | None
Prevention of Nausea and Vomiting Associated with Moderately Emetogenic Cancer Chemotherapy and Combinations of Anthracycline and Cyclophosphamide
VARUBI | 180 mg as a single dose orally within 2 hours prior to initiation of chemotherapy | None
Dexamethasone | 20 mg; 30 min prior to initiation of chemotherapy | None
5-HT3 receptor antagonist | See the prescribing information for the co-administered 5-HT3 receptor antagonist for appropriate dosing information. | See the prescribing information for the co-administered 5-HT3 receptor antagonist for appropriate dosing information.

3 DOSAGE FORMS AND STRENGTHS

Tablets: 90 mg rolapitant; film-coated, blue capsule shaped, debossed with T0101 on one side and 100 on the other side.

4 CONTRAINDICATIONS

VARUBI is contraindicated in patients taking CYP2D6 substrates with a narrow therapeutic index, such as thioridazine and pimozide. VARUBI can significantly increase the plasma concentrations of thioridazine and pimozide, which may result in QT prolongation and Torsades de Pointes [see Warnings and Precautions (5.1)].

VARUBI is contraindicated in pediatric patients less than 2 years of age because of irreversible impairment of sexual development and fertility observed in juvenile rats at clinically relevant dosages [see Use in Specific Populations (8.4)].

5 WARNINGS AND PRECAUTIONS

5.1 Interaction with CYP2D6 Substrates

Rolapitant is a moderate inhibitor of CYP2D6. Exposure to dextromethorphan, a CYP2D6 substrate, following a single dose of rolapitant increased about 3-fold on Days 8 and Day 22. The inhibition of CYP2D6 persisted on Day 28 with a 2.3-fold increase in dextromethorphan (CYP2D6 substrate) concentrations, the last time point measured. The inhibitory effect of rolapitant on CYP2D6 is expected to persist beyond 28 days for an unknown duration following administration of VARUBI [see Drug Interactions (7), Clinical Pharmacology (12.3)].

Narrow Therapeutic Index Drugs (Thioridazine and Pimozide)

VARUBI is contraindicated in patients taking CYP2D6 substrates with a narrow therapeutic index such as thioridazine and pimozide. Increased plasma concentrations of thioridazine and pimozide are associated with serious and/or life-threatening events of QT prolongation and Torsades de Pointes [see Contraindications (4)].

Before starting treatment with VARUBI, consider whether patients require treatment with thioridazine or pimozide. If patients require these drugs, use an alternative antiemetic to VARUBI or an alternative to thioridazine or pimozide that is not metabolized by CYP2D6.

Other Drugs

VARUBI can also increase plasma concentrations of other CYP2D6 substrates for at least 28 days following administration of VARUBI and may result in adverse reactions.

Before starting treatment with VARUBI, consult the prescribing information for CYP2D6 substrates to obtain additional information about interactions with CYP2D6 inhibitors.

6 ADVERSE REACTIONS

The following adverse reactions are discussed in greater detail in other sections of the labeling:

- Interaction with CYP2D6 Substrates [see Contraindications (4), Warnings and Precautions (5.1)]

6.1 Clinical Trials Experience

Because clinical trials are conducted under widely varying conditions, adverse reaction rates observed in the clinical trials of a drug cannot be directly compared to rates in the clinical trials of another drug and may not reflect the rates observed in clinical practice.

In 4 controlled clinical trials in patients receiving emetogenic cancer chemotherapy, VARUBI was given in combination with a 5-HT3 receptor antagonist and dexamethasone. On Day 1 of Cycle 1 of chemotherapy, 1567 patients were treated with VARUBI and 1198 of these patients continued into the optional multiple cycle extension for up to 6 cycles of chemotherapy. The median number of cycles administered 180 mg of VARUBI was four. VARUBI 180 mg was administered to 1294 patients.

In Cycle 1 adverse reactions were reported in approximately 7% of patients treated with VARUBI compared with approximately 6% of patients treated with control therapy. The most common adverse reactions reported with an incidence of ≥3% and greater than control are listed in Table 2 and Table 3.

Table 2: Most Common Adverse Reactions in Patients Receiving Cisplatin-Based Highly Emetogenic Chemotherapy (Cycle 1)*
 | VARUBI Regimen (VARUBI, Dexamethasone, and 5-HT 3 Receptor Antagonist) N = 624 | Control (Placebo, Dexamethasone, and 5-HT 3 Receptor Antagonist) N = 627
Neutropenia | 9% | 8%
Hiccups | 5% | 4%
Abdominal Pain | 3% | 2%
* all reactions occurring at ≥3% in the VARUBI group and for which the rate for VARUBI exceeds the rate for control

Table 3: Most Common Adverse Reactions in Patients Receiving Moderately Emetogenic Chemotherapy and Combinations of Anthracycline and Cyclophosphamide (Cycle 1)*
 | VARUBI Regimen (VARUBI, Dexamethasone, and 5-HT 3 Receptor Antagonist) N = 670 | Control (Placebo, Dexamethasone, and 5-HT 3 Receptor Antagonist) N = 674
Decreased appetite | 9% | 7%
Neutropenia | 7% | 6%
Dizziness | 6% | 4%
Dyspepsia | 4% | 2%
Urinary tract infection | 4% | 3%
Stomatitis | 4% | 2%
Anemia | 3% | 2%
*all reactions occurring at ≥3% in the VARUBI group and for which the rate for VARUBI exceeds the rate for control.

Adverse reactions in the multiple-cycle extensions of highly and moderately emetogenic chemotherapy studies for up to 6 cycles of chemotherapy were generally similar to that observed in Cycle 1.

7 DRUG INTERACTIONS

Rolapitant is a moderate CYP2D6 inhibitor. The inhibition of CYP2D6 persisted on Day 28 with a 2.3-fold increase in dextromethorphan concentrations, the last time point measured. The inhibitory effect of rolapitant on CYP2D6 is expected to persist beyond 28 days for an unknown duration following administration of VARUBI [see Clinical Pharmacology (12.3)].

Oral rolapitant is an inhibitor of Breast-Cancer-Resistance Protein (BCRP) and p-glycoprotein (P-gp). Rolapitant, given as a single oral dose, is not an inhibitor or inducer of CYP3A4 [see Clinical Pharmacology (12.3)]. Therefore, no dosage adjustment for dexamethasone (CYP3A4 substrate) is needed when co-administered with VARUBI [see Dosage and Administration (2)].

Table 4 and Table 5 include drugs with clinically important drug interactions when administered concomitantly with VARUBI and instructions for preventing or managing them.

Table 4: Clinically Relevant Interactions Affecting Drugs Co-Administered with VARUBI
CYP2D6 Substrates
Narrow Therapeutic Index Drugs (Thioridazine and Pimozide)
Clinical Impact: | Increased plasma concentrations of thioridazine and pimozide are associated with serious and/or life-threatening events of QT prolongation and Torsades de Pointes.
Intervention: | VARUBI is contraindicated in patients taking CYP2D6 substrates with a narrow therapeutic index such as thioridazine and pimozide. If patients require these drugs, use an alternative antiemetic to VARUBI or an alternative to thioridazine or pimozide that is not metabolized by CYP2D6 [see Contraindications (4), Warnings and Precautions (5.1)].
Other CYP2D6 Substrates
Clinical Impact: | VARUBI can increase plasma concentrations of other CYP2D6 substrates for at least 28 days following administration of VARUBI and may result in adverse reactions. Before starting treatment with VARUBI consult the prescribing information of CYP2D6 substrates to obtain further information about interactions with CYP2D6 inhibitors [see Clinical Pharmacology (12.3)].
Intervention: | Before starting treatment with VARUBI consult the prescribing information of CYP2D6 substrates to obtain further information about interactions with CYP2D6 inhibitors [see Warnings and Precautions (5.1)].
BCRP Substrates with a Narrow Therapeutic Index (e.g., methotrexate, topotecan, or irinotecan)
Clinical Impact: | Increased plasma concentrations of BCRP substrates (e.g., methotrexate, topotecan, or irinotecan) may result in potential adverse reactions [see Clinical Pharmacology (12.3)].
Intervention: | Monitor for adverse reactions related to the concomitant drug if use of VARUBI cannot be avoided. Use the lowest effective dose of rosuvastatin (see prescribing information for additional information on recommended dosing).
P-gp Substrates with a Narrow Therapeutic Index (e.g. digoxin)
Clinical Impact: | Increased plasma concentrations of P-gp substrates (e.g., digoxin) may result in potential adverse reactions [see Clinical Pharmacology (12.3)].
Intervention: | Monitor digoxin concentrations with concomitant use of VARUBI and adjust the dosage as needed to maintain therapeutic concentrations. Monitor for adverse reactions if concomitant use of VARUBI with other P-gp substrates with a narrow therapeutic index cannot be avoided.
Warfarin
Clinical Impact: | Although co-administration of intravenous rolapitant (VARBI is not approved for intravenous use), which has a higher Cmax than oral VARUBI, with warfarin did not substantially increase the systemic exposure to S-warfarin, the active enantiomer, the effects on INR and prothrombin time were not studied [see Clinical Pharmacology (12.3)].
Intervention: | Monitor INR and prothrombin time and adjust the dosage of warfarin, as needed with concomitant use of VARUBI, to maintain the target INR range.

Table 5: Clinically Relevant Interactions Affecting Rolapitant When Co-Administered with Other Drugs
Strong CYP3A4 Inducers (e.g. rifampin)
Clinical Impact: | Co-administration of VARUBI with rifampin can significantly reduce the plasma concentrations of rolapitant and decrease the efficacy of VARUBI [see Clinical Pharmacology (12.3)].
Intervention: | Avoid the use of VARUBI in patients who require chronic administration of strong CYP3A4 inducers.

8 USE IN SPECIFIC POPULATIONS

8.1 Pregnancy

Risk Summary

The limited data with VARUBI use in pregnant women are insufficient to inform a drug associated risk of adverse developmental outcomes. In animal reproduction studies, there were no adverse developmental effects observed with oral administration of rolapitant in rats and rabbits during the period of organogenesis at doses up to 1.2 times and 2.9-times, respectively, the maximum recommended human dose (MRHD) (see Data).

The estimated background risk of major birth defects and miscarriage for the indicated population is unknown. All pregnancies have a background risk of birth defect, loss, or other adverse outcomes. In the U.S. general population, the estimated background risk of major birth defects and miscarriage in clinically recognized pregnancies is 2 to 4% and 15 to 20%, respectively.

Data

Animal Data

The potential embryo-fetal toxicity of rolapitant was assessed in pregnant rats administered oral doses up to 22.5 mg/kg per day throughout the period of organogenesis. Rats administered doses of 13.5 or 22.5 mg/kg per day rolapitant exhibited evidence of maternal toxicity including decreased body weight gain and/or body weight loss and a concomitant decrease in food consumption during the first week of dosing. No adverse embryo-fetal developmental effects were observed at doses up to 22.5 mg/kg per day rolapitant (approximately 1.2 times the recommended human dose on a body surface area basis). In rabbits administered rolapitant throughout the period of organogenesis, oral doses up to 27 mg/kg per day (approximately 2.9 times the recommended human dose on a body surface area basis) were without effects on the developing fetus.

The pre- and postnatal developmental effects of rolapitant were assessed in rats administered oral doses of 2.25, 9 or 22.5 mg/kg per day during the periods of organogenesis and lactation. Maternal toxicity was evident based on mortality/moribund condition, decreased body weight and food consumption, total litter loss, prolonged parturition, decreased length of gestation, and increased number of unaccounted for implantation sites at a dose of 22.5 mg/kg per day (approximately 1.2 times the recommended human dose on a body surface area basis). Effects on offspring at this dose included decreased postnatal survival, and decreased body weights and body weight gain, and may be related to the maternal toxicity observed. At a maternal dose of 9 mg/kg per day rolapitant (approximately 0.5 times the recommended human dose on a body surface area basis), there was a decrease in memory in female pups in a maze test and a decrease in pup body weight.

8.2 Lactation

Risk Summary

There are no data on the presence of rolapitant in human milk, the effects of rolapitant in the breastfed infant, or the effects of rolapitant on milk production. Rolapitant administered orally to lactating female rats was present in milk (see Data). The developmental and health benefits of breastfeeding should be considered along with the mother's clinical need for VARUBI and any potential adverse effects on the breastfed infant from VARUBI or from the underlying maternal condition or the use of concomitant chemotherapy.

Data

Radioactivity from labeled [^14C] rolapitant was transferred into milk of lactating rats following a single oral dose of 22.5 mg/kg, and the maximum radioactivity in milk was observed at 12 hours post-dose. The mean milk/plasma radioactivity concentration ratios in dams at 1 to 48 hours post-dose ranged from 1.24 to 3.25. Based on average daily consumption of milk (2 mL/day) and the maximum milk radioactivity determined, pup exposure is expected to be 0.3% of the orally administered dose.

8.3 Females and Males of Reproductive Potential

Infertility

Females

In animal fertility studies, rolapitant impaired the fertility in females in a reversible fashion [see Nonclinical Toxicology (13.1)].

8.4 Pediatric Use

The safety and effectiveness of VARUBI have not been established in pediatric patients. VARUBI is contraindicated in pediatric patients less than 2 years of age [see Contraindications(4)]. Rolapitant administration in juvenile rats (human age equivalent of birth to 2 years) resulted in abnormal ovarian and uterine development, early sexual development in females, delayed sexual development in males, and impaired fertility.

Juvenile Animal Toxicity Data

A toxicity study in juvenile rats at rolapitant doses approximately 1.2 and 2.5 times the approved adult body surface area (BSA)-based dose from postnatal day (PND) 7 through PND 70 (approximate human age equivalent of birth to 16 years) identified reproductive toxicity. A subsequent toxicity study in juvenile rats was conducted to identify the critical window of exposure for reproductive toxicity. A rolapitant dose of 50 mg/kg/day (approximately 2.7 times the approved adult BSA-based dose) was administered daily from PNDs 7 through 70, 7 to 21, 21 to 42 and 42 to 70 (approximate human age equivalent of birth to 16 years, birth to 2 years, 2 years to 12 years, and 12 years to 16 years, respectively). Female juvenile rats treated with rolapitant beginning on PND 7 developed adverse effects including partial or irreversible lower uterine weights that correlated with decreased endometrial glands of the uterus, decreases in the numbers of corpora lutea, implantation sites and live embryos and increases in pre- and post-implantation loss, and early resorptions. These adverse effects were observed in female juvenile rats administered rolapitant prior to PND 21 (approximate human age equivalent of 2 years). Additionally, juvenile rats treated with rolapitant beginning on either PND 7 or PND 21 developed slight changes in the onset of sexual maturation (including earlier attainment of vaginal opening in females and delay in preputial separation in males).

8.5 Geriatric Use

Of the 1294 subjects treated with VARUBI, 25% were 65 years and over, while 5% were 75 and over. No overall differences in safety or efficacy were reported between the elderly subjects and younger subjects, but greater sensitivity of some older individuals cannot be ruled out.

8.6 Hepatic Impairment

No dosage adjustment is needed in patients with mild (Child-Pugh Class A) or moderate (Child-Pugh Class B) hepatic impairment. There are no clinical or pharmacokinetic data in patients with severe hepatic impairment (Child-Pugh Class C). Avoid use of VARUBI in patients with severe hepatic impairment. If use cannot be avoided, monitor patients for adverse reactions related to rolapitant [see Adverse Reactions (6.1)].

10 OVERDOSAGE

There are no data on overdose with VARUBI.

There is no antidote for VARUBI overdose. Discontinue VARUBI in the event of overdose, and institute general supportive measures and close observation.

11 DESCRIPTION

VARUBI contains rolapitant, a substance P/neurokinin 1 (NK1) receptor antagonist. Rolapitant hydrochloride is chemically described as (5S,8S)-8- { [(1R)-1-[3,5-bis(trifluoromethyl)phenyl]ethoxy]methyl]}-8-phenyl-1,7-diazaspiro[4.5]decan-2-one hydrochloride. Its empirical formula is C25H26F6N2O2. HCl.H2O, and its structural formula is:

rolapitant hydrochloride

Rolapitant hydrochloride is a white to off-white powder, with a molecular weight of 554.95. Solubility of rolapitant hydrochloride in aqueous solution is pH-dependent and is more soluble at lower pH. Rolapitant has good solubility in common pharmaceutical solvents such as ethanol, propylene glycol and 40% hydroxypropyl beta-cyclodextrin.

Each tablet contains 90 mg rolapitant (equivalent to 100 mg rolapitant hydrochloride) and the following inactive ingredients: colloidal silicon dioxide, croscarmellose sodium, lactose monohydrate, magnesium stearate, microcrystalline cellulose, povidone, and pregelatinized starch. The tablets are coated in non-functional blue and clear coats. The tablet coating comprises the following inactive ingredients: FD&C Blue No. 2-Indigo Carmine Lake, polyethylene glycol, polysorbate 80, polyvinyl alcohol, talc, and titanium dioxide.

12 CLINICAL PHARMACOLOGY

12.1 Mechanism of Action

Rolapitant is a selective and competitive antagonist of human substance P/NK1 receptors. Rolapitant does not have significant affinity for the NK2 or NK3 receptors or for a battery of other receptors, transporters, enzymes and ion channels. Rolapitant is also active in animal models of chemotherapy-induced emesis.

12.2 Pharmacodynamics

NK1 Receptor Occupancy

A human Positron Emission Tomography (PET) study with rolapitant demonstrated that rolapitant crosses the blood brain barrier and occupies brain NK1 receptors. A dose-dependent increase in mean NK1 receptor occupancy was observed in the oral dose range from 4.5 mg to 180 mg of rolapitant. At the 180 mg oral dose of rolapitant, the mean NK1 receptor occupancy was 73% in the striatum at 120 hours after a single dose administration in healthy subjects. The relationship between NK1 receptor occupancy and the clinical efficacy of rolapitant has not been established.

Cardiac Electrophysiology

At an oral dose of 720 mg (4 times the recommended oral dose), VARUBI does not prolong the QT interval to any clinically relevant extent.

12.3 Pharmacokinetics

Absorption

Following a single oral dose administration of 180 mg VARUBI under fasting conditions to healthy subjects, rolapitant was measurable in plasma within 30 minutes and the peak plasma concentration (Cmax) for rolapitant which was reached in about 4 hours and mean Cmax was 968 ng/mL (%CV:28%).

Following multiple oral doses of 9 to 45 mg once daily of rolapitant (5% to 25% of the recommended dose) for 10 days, accumulation of rolapitant (ratio of AUC0-24hr) ranged from 5.0 to 5.3 fold.

The systemic exposures (Cmax and AUC) to rolapitant increased in a dose-proportional manner when single oral doses of rolapitant increased from 4.5 mg to 180 mg. With 4 times the recommended clinical oral dose of 180 mg, the Cmax and AUC of rolapitant increased 3.1 fold and 3.7 fold, respectively.

Concomitant administration of a high-fat meal did not significantly affect the pharmacokinetics of rolapitant after administration of 180 mg VARUBI [see Dosage and Administration (2)].

Distribution

Rolapitant was highly protein bound to human plasma (99.8%). The apparent volume of distribution (Vd/F) following a single oral dose of 180 mg rolapitant was 460 L in healthy subjects. The large Vd indicated an extensive tissue distribution of rolapitant. In a population pharmacokinetic analysis of oral rolapitant, the Vd/F was 387 L in cancer patients.

Elimination

Following single oral doses (4.5 to 180 mg) of rolapitant, the mean terminal half-life (t1/2) of rolapitant ranged from 169 to 183 hours (approximately 7 days), and was independent of dose. In a population pharmacokinetic analysis, the apparent total clearance (CL/F) of oral rolapitant was 0.96 L/hour in cancer patients.

Metabolism

Rolapitant is metabolized primarily by CYP3A4 to form a major active metabolite, M19 (C4-pyrrolidine-hydroxylated rolapitant). In a mass balance study, the metabolite M19 was determined to be the major circulating metabolite. The rate of formation of M19 was relatively slow, resulting in the delayed median Tmax of 120 hours (range: 24 to 168 hours) with Cmax of 183 ng/mL. The mean half-life of M19 was 158 hours.

The exposure ratio of M19 to rolapitant was approximately 50% in plasma.

Excretion

Rolapitant is eliminated primarily through the hepato/biliary route. Following administration of a single oral 180-mg dose of [^14C]-rolapitant, on average 14.2% (range 9% to 20%) and 73% (range 52% to 89%) of the dose was recovered in the urine and feces, respectively over 6 weeks. In pooled samples collected over 2 weeks, 8.3% of the dose was recovered in the urine primarily as metabolites and 37.8% of the dose was recovered in the feces primarily as unchanged rolapitant. Unchanged rolapitant or M19 was not found in pooled urine sample.

Specific Populations

Age, Male and Female Patients and Racial or Ethnic Groups

Population pharmacokinetic analyses indicated that age, sex and race had no significant impact on the pharmacokinetics of rolapitant.

Patients with Hepatic Impairment

Following administration of a single oral dose of 180 mg rolapitant to patients with mild hepatic impairment (Child-Pugh Class A), the pharmacokinetics of rolapitant were comparable with those of healthy subjects. In patients with moderate hepatic impairment (Child-Pugh Class B), the mean Cmax was 25% lower while mean AUC of rolapitant was similar compared to those of healthy subjects. The median Tmax for M19 was delayed to 204 hours in patients with mild or moderate hepatic impairment compared to 168 hours in healthy subjects. The pharmacokinetics of rolapitant were not studied in patients with severe hepatic impairment (Child-Pugh Class C) [see Use in Specific Populations (8.6)].

Patients with Renal Impairment

In population pharmacokinetic analyses, rolapitant pharmacokinetics in cancer patients with mild (CLcr: 60 to 90 mL/min) or moderate (CLcr: 30 to 60 mL/min) renal impairment was comparable to cancer patients with normal kidney function. Information is insufficient for the effect of severe renal impairment. The pharmacokinetics of rolapitant was not studied in patients with end-stage renal disease requiring hemodialysis.

Drug Interaction Studies

Effect of Other Drugs on Rolapitant

Rolapitant is a substrate for CYP3A4.

CYP3A4 inducers
When 600 mg rifampin was administered once daily for 7 days before and 7 days after administration of a single oral dose of 180 mg rolapitant, the mean Cmax of rolapitant was reduced by 30% and the mean AUC was reduced by 85% compared to administration of rolapitant alone. The mean half-life of rolapitant decreased from 176 hours without rifampin to 41 hours with concurrent rifampin [see Drug Interactions (7)].

CYP3A4 inhibitors
Concurrent administration of 400 mg ketoconazole, a strong CYP3A4 inhibitor, once daily for 21 days following a single 90 mg oral dose of rolapitant, did not affect the Cmax of rolapitant while the AUC increased by 21%. These pharmacokinetic differences are not clinically significant.

Effect of Rolapitant on Other Drugs

The effect of VARUBI on CYP450 enzymes and transporters is summarized below.

CYP3A4 substrates
Rolapitant is neither an inhibitor nor an inducer of CYP3A4.
Midazolam: A single oral dose of 180 mg rolapitant had no significant effects on the pharmacokinetics of midazolam when oral midazolam 3 mg was co-administered on Day 1 and administered alone on Days 6 and 9.
Ondansetron: Rolapitant had no significant effects on the pharmacokinetics of intravenous ondansetron when concomitantly administered with a single 180 mg oral dose of rolapitant on the same day.
Dexamethasone: Rolapitant had no significant effects on the pharmacokinetics of dexamethasone when oral dexamethasone was administered on Days 1 to 3 after a single 180 mg oral dose of rolapitant was co-administered on Day 1 [see Dosage and Administration (2)].

CYP2D6 substrates
Rolapitant is a moderate inhibitor of CYP2D6 [see Contraindications (4), Warnings and Precautions (5.1), and Drug Interactions (7)].
Following a single dose of oral rolapitant, the AUC of dextromethorphan (CYP2D6 substrate) increased 2.6-fold on Day 1 and 3.3-fold on Day 8 and was similar to that following a single dose of intravenous rolapitant (VARUBI is not approved for intravenous use). Following intravenous rolapitant, inhibition of CYP2D6 continued with approximately a 3-fold increase in the AUC of dextromethorphan on Days 15 and 22 and attenuated to a 2.3-fold increase from Day 22 to Day 28, the last time point measured. See Table 6 for the summary of effects of oral and intravenous rolapitant on dextromethorphan.

Table 6: Effect of Oral and Intravenous Rolapitant on the Systemic Exposure of Co-Administered CYP2D6 Substrate (Dextromethorphan)
Rolapitant Dose (route of administration) | % Change for Dextromethorphan
Rolapitant Dose (route of administration) | Day 1 with Rolapitant |  | Day 8 without Rolapitant |  | Day 15 without Rolapitant |  | Day 22 without Rolapitant |  | Day 29 without Rolapitant
Rolapitant Dose (route of administration) | Change in Cmax | Change in AUC | Change in Cmax | Change in AUC | Change in Cmax | Change in AUC | Change in Cmax | Change in AUC | Change in Cmax | Change in AUC
180 mga (Oral) | 120% ↑ | 160% ↑ | 180% ↑ | 230% ↑ | N/A
166.5 mgb (Intavenous) | 75% ↑ | 110% ↑ | 140% ↑ | 220% ↑ | 170% ↑ | 220% ↑ | 120% ↑ | 180% ↑ | 96% ↑ | 130% ↑
a A single oral dose of 180 mg rolapitant was administered on Day 1; the interacting drug (dextromethorphan 30 mg) was administered orally on Day 1 with rolapitant and alone on Day 8.
b A single intravenous dose of 166.5 mg rolapitant was administered on Day 1; the interacting drug (dextromethorphan 30 mg) was administered orally on Day 1 with rolapitant and alone on Days 8, 15, 22, and 29. VARUBI is not approved for intravenous use. The AUC of rolapitant following single intravenous dose of 166.5 mg is similar to that following single oral dose of VARUBI 180 mg.
↑ Denotes a mean increase in exposure by the percentage indicated.
N/A: not applicable

BCRP Transporter
In vitro, rolapitant is a BCRP transporter inhibitor.
When sulfasalazine (BCRP substrate) was administered with a single oral dose of 180 mg rolapitant on Day 1 and without rolapitant on Day 8, a 140% increase in Cmax and a 130% increase in AUC of sulfasalazine 500 mg was observed on Day 1, a 17% increase in Cmax and a 32% increase in AUC was observed on Day 8 [see Drug Interactions (7)].

P-glycoprotein substrates
In vitro, rolapitant is a P-gp inhibitor.
When digoxin (P-gp substrate) was administered with a single oral dose of 180 mg rolapitant, a 70% increase in Cmax and a 30% increase in AUC of digoxin 0.5 mg were observed [see Drug Interactions (7)].

Warfarin
When warfarin was administered with a single intravenous dose of 166.5 mg rolapitant, 3% and 18% increases in Cmax and AUC of S-warfarin were observed on Day 1, respectively. On Day 8, the increases were 3% for Cmax and 21% for AUC. The effect on INR or prothrombin time was not measured. Of note, Cmax was greater with intravenous rolapitant when compared to oral VARUBI [see Drug Interactions (7)].

Substrates for other CYP enzymes
In vitro studies suggest that rolapitant is not an inhibitor of CYP1A2 and CYP2E1. In vitro studies suggest that rolapitant inhibits CYP2A6; however, a clinically meaningful drug interaction via an inhibition of CYP2A6 appears unlikely.
No clinically significant interaction was seen on the systemic exposures of the following drugs when administered with a single oral dose of 180 mg rolapitant on Day 1: repaglinide (CYP2C8 substrate; no effect on repaglinide 0.25 mg on Day 1; on Day 8: 29% and 24% increase in Cmax and AUC, respectively), efavirenz (CYP2B6 substrate; 18% decrease in Cmax and no effect on AUC of efavirenz 600 mg on Day 1; on Day 8: no effect on Cmax and 28% increase in AUC), tolbutamide (CYP2C9 substrate; no effect on tolbutamide 500 mg on Day 1 and on Day 8), or omeprazole (CYP2C19 substrate; 44% increase in Cmax and 23% increase in AUC of omeprazole 40 mg on Day 1; on Day 8: 37% and 15% increase in Cmax and AUC, respectively).

Substrates for other transporters
In vitro studies suggest that oral rolapitant is unlikely to inhibit organic anion transporting polypeptides 1B1 and 1B3 (OATP1B1 and OATP1B3), organic anion transporters 1 and 3 (OAT1 and OAT3), organic cation transporter 2 (OCT2), and multidrug and toxin extrusion proteins 1 and 2K (MATE1 and MATE2K) in vivo.

13 NONCLINICAL TOXICOLOGY

13.1 Carcinogenesis, Mutagenesis, Impairment of Fertility

Carcinogenesis

The carcinogenic potential of rolapitant was assessed in 2-year carcinogenicity studies in CD-1 mice and Sprague-Dawley rats. In mice, there were no drug-related neoplastic findings at doses up to 135 mg/kg per day (approximately 3.6 times the recommended human dose on a body surface area basis). In rats, there were no drug-related neoplastic findings at doses up to 90 mg/kg per day (approximately 4.9 times the recommended human dose on a body surface area basis).

Mutagenesis

Rolapitant was not genotoxic in an Ames test, a human peripheral blood lymphocyte chromosome aberration test, and a mouse micronucleus test.

Impairment of Fertility

In a fertility and early embryonic development study in female rats, rolapitant at an oral dose of 9 mg/kg per day (approximately 0.5 times the recommended human dose on a body surface area basis) caused a transient decrease in maternal body weight gain and increases in the incidence of pre- and post-implantation loss. At a rolapitant dose of 4.5 mg/kg per day (approximately 0.2 times the recommended human dose on a body surface area basis), there were slight decreases in the number of corpora lutea and implantation sites. Rolapitant did not affect the fertility or general reproductive performance of male rats at doses up to 90 mg/kg per day(approximately 4.9 times the recommended human dose on a body surface area basis). Reversibility in female rats was demonstrated in a follow-up study.

14 CLINICAL STUDIES

Cisplatin-Based Highly Emetogenic Chemotherapy (HEC)

In two multicenter, randomized, double-blind, parallel group, controlled clinical studies (Study 1 and Study 2), the VARUBI regimen (VARUBI, granisetron and dexamethasone) was compared with control therapy (placebo, granisetron and dexamethasone) in patients receiving a chemotherapy regimen that included cisplatin >60 mg/m^2. See Table 7 for the treatment regimens.

Table 7: Treatment Regimens in Studies 1 and 2
 | Day 1 | Day 2 to 4
VARUBI Regimen
Oral VARUBIa | 180 mg | None
Oral Dexamethasone | 20 mgb | 8 mg twice daily
Intravenous Granisetron | 10 mcg/kgc | None
Control Regimend
Oral Dexamethasone | 20 mgb | 8 mg twice daily
Intravenous Granisetron | 10 mcg/kgc | None
a VARUBI was administered 1 to 2 hours prior to chemotherapy treatment on Day 1.
b Dexamethasone was administered 30 minutes prior to chemotherapy on Day 1. There is no drug interaction between VARUBI and dexamethasone, so no dosage adjustment for dexamethasone is required [see Clinical Pharmacology (12.3)].
c The dose of granisetron was administered 30 minutes prior to chemotherapy on Day 1.
d VARUBI placebo was used to maintain blinding.

Study 1

A total of 532 patients were randomized to either the VARUBI regimen (N=266) or control therapy (N=266). A total of 526 patients were included in the evaluation of efficacy. Of those randomized 42% were women, 58% men, 67% White, 23% Asian, 1% Black, and 9% multi-racial/other/unknown. The proportion of patients from North America was 16%. Patients in this clinical study ranged from 20 to 90 years of age, with a mean age of 57 years. In Study 1, 26% of patients were 65 years or older, with 3% of patients being 75 years or older. The mean cisplatin dose was 77 mg/m^2.

During this study, 82% of the patients received a concomitant chemotherapeutic agent in addition to protocol-mandated cisplatin. The most common concomitant chemotherapeutic agents administered during Cycle 1 were: gemcitabine (17%), paclitaxel (12%), fluorouracil (11%), etoposide (10%), vinorelbine (9%), docetaxel (9%), pemetrexed (7%), doxorubicin (6%) and cyclophosphamide (5%).

Study 2

A total of 555 patients were randomized to either the VARUBI regimen (N=278) or control therapy (N=277). A total of 544 patients were included in the evaluation of efficacy. Of those randomized 32% were women, 68% men, 81% White, 14% Asian, 1% Black, and 5% multi-racial/other/unknown. The proportion of patients from North America was 7%. Patients in this clinical study ranged from 18 to 83 years of age, with a mean age of 58 years. In this study, 27% of patients were 65 years or older, with 3% of patients being 75 years or older. The mean cisplatin dose was 76 mg/m^2.

During this study, 85% of the patients received a concomitant chemotherapeutic agent in addition to protocol-mandated cisplatin. The most common concomitant chemotherapeutic agents administered during Cycle 1 were: vinorelbine (16%), gemcitabine (15%), fluorouracil (12%), etoposide (11%), pemetrexed (9%), docetaxel (7%), paclitaxel (7%), epirubicin (5%) and capecitabine (4%).

The primary endpoint in both studies was complete response (defined as no emetic episodes and no rescue medication) in the delayed phase (25 to 120 hours) of chemotherapy-induced nausea and vomiting.

Moderately Emetogenic Chemotherapy (MEC) and Combinations of Anthracycline and Cyclophosphamide Chemotherapy

Study 3

In Study 3, a multicenter, randomized, double-blind, parallel group, controlled clinical study in moderately emetogenic chemotherapy, the VARUBI regimen (VARUBI, granisetron and dexamethasone) was compared with control therapy (placebo, granisetron and dexamethasone) in patients receiving a moderately emetogenic chemotherapy regimen that included at least 50% of patients receiving a combination of anthracycline and cyclophosphamide. The percentage of patients who received carboplatin in Cycle 1 was 30%. Treatment regimens for the VARUBI and control arms are summarized in Table 8.

Table 8: Treatment Regimens in Study 3
 | Day 1 | Day 2 to 3
VARUBI Regimen
Oral VARUBIa | 180 mg | none
Oral Dexamethasone | 20 mgb | none
Oral Granisetron | 2 mgb | 2 mg once daily
Control Regimend
Oral Dexamethasone | 20 mgb | none
Oral Granisetron | 2 mgc | 2 mg once daily
a VARUBI was administered 1 to 2 hours prior to chemotherapy treatment on Day 1.
b Dexamethasone was administered 30 minutes prior to chemotherapy on Day 1. There is no drug interaction between VARUBI and dexamethasone, so no dosage adjustment for dexamethasone is required [see Clinical Pharmacology (12.3)].
c The dose of granisetron was administered 30 minutes prior to chemotherapy on Day 1.
d VARUBI placebo was used to maintain blinding.

A total of 1369 patients were randomized to either the VARUBI regimen (N=684) or control therapy (N=685). A total of 1332 patients were included in the evaluation of efficacy. Of those randomized 80% were women, 20% men, 77% White, 13% Asian, 4% Black, and 6% multi-racial/other/unknown. The proportion of patients from North America was 33%. Patients in this clinical study ranged from 22 to 88 years of age, with a mean age of 57 years. In this study, 28% of patients were 65 years or older, with 7% of patients being 75 years or older.

The primary endpoint was complete response (defined as no emetic episodes and no rescue medication) in the delayed phase (25 to 120 hours) of chemotherapy-induced nausea and vomiting.

A summary of the study results from HEC Studies 1 and 2 and for the MEC Study 3 is shown in Table 9.

Table 9: Percent of Patients Receiving Emetogenic Chemotherapy Responding by Treatment Group for the HEC Studies 1 and 2 and for the MEC Study 3
Endpoint | HEC Study 1 |  |  | HEC Study 2 |  |  | MEC Study 3
 | VARUBIa (N=264) Rate (%) | Controla (N=262) Rate (%) | P-Value Treatment Difference (95% C.I.) | VARUBIa (N=271) Rate (%) | Controla (N=273) Rate (%) | P-Value Treatment Difference (95% C.I.) | VARUBIa (N=666) Rate (%) | Controla (N=666) Rate (%) | P-Value Treatment Difference (95% C.I.)
Primary Endpoint: Complete Response in the Delayed Phase | 72.7 | 58.4 | <0.001b 14.3 (6.3, 22.4) | 70.1 | 61.9 | 0.043 b 8.2 (0.3, 16.1) | 71.3 | 61.6 | <0.001b 9.8 (4.7, 14.8)
a Granisetron and dexamethasone were used as concomitant drugs.
b Results were obtained based on the Cochran-Mantel-Haenszel test stratified by gender.

Multiple-Cycle Extension: In Studies 1, 2, and 3, patients had the option of continuing into a multiple-cycle extension for up to 5 additional cycles of chemotherapy receiving the same treatment as assigned in cycle 1. At Day 6 to 8 following initiation of chemotherapy, patients were asked to recall whether they had any episode of vomiting or retching or nausea that interfered with normal daily life. The results are summarized by study and treatment group in Figure 1 below.

Figure 1: No Emesis and No Nausea Interfering with Daily Life over Cycles 2-6

Study 1

Study 2

Study 3

16 HOW SUPPLIED/STORAGE AND HANDLING

VARUBI is available as film-coated, capsule shaped, blue tablets, debossed with T0101 on one side and 100 on the other side. Each tablet contains 90 mg rolapitant. VARUBI is packaged in an Aclar blister shell with aluminum foil backing and supplied as follows:

NDC 70720-101-02 | A single dose child-resistant wallet (2 tablets as one set of twinned blisters)

Store at 20ºC to 25ºC (68ºF to 77ºF); excursions permitted to 15°C to 30°C (59°F to 86°F) [see USP Controlled Room Temperature].

17 PATIENT COUNSELING INFORMATION

Advise the patient to read the FDA-approved patient labeling (Patient Information).

Drug Interactions

Advise patients to tell their healthcare provider when they start or stop taking any concomitant medications. VARUBI is a moderate CYP2D6 inhibitor and can increase plasma concentrations of CYP2D6 substrates [see Contraindications (4), Warnings and Precautions (5.1), Drug Interactions (7)].

Infertility

Advise females of reproductive potential that VARUBI may impair fertility [see Use in Specific Populations (8.3), Nonclinical Toxicology (13.1)].

Manufactured for: TerSera Therapeutics LLC, Deerfield, IL 60015

©2020 TerSera Therapeutics LLC

PATIENT INFORMATION
VARUBI® (vuh ROO bee)
(rolapitant)
tablets, for oral use

What is VARUBI?

- VARUBI is a prescription medicine called an “antiemetic.” VARUBI is used with other medicines in adults to help prevent nausea and vomiting that happens later with certain anti-cancer medicines (chemotherapy).
- It is not known if VARUBI is safe and effective in children.

Do not take VARUBI if you:

- take thioridazine or pimozide. Taking VARUBI with thioridazine or pimozide can cause serious or life-threatening heart rhythm changes.
- are a child less than 2 years of age.

Before taking VARUBI, tell your doctor about all of your medical conditions, including if you:

- have liver problems.
- are pregnant or plan to become pregnant. It is not known if VARUBI will harm your unborn baby. VARUBI may affect the ability to have a child (fertility problems) in females.
- are breastfeeding or plan to breastfeed. It is not known if VARUBI passes into your breast milk or could harm your baby. Talk to your doctor about the best way to feed your baby if you take VARUBI.

Tell your doctor about all the medicines you take or stop taking, including prescription and over-the-counter medicines, vitamins, and herbal supplements. Keep a list of your medicines to show your doctor and pharmacist when you get a new medicine.
VARUBI and other medicines may affect each other and could cause serious side effects.

How should I take VARUBI?

- Take VARUBI exactly as your doctor tells you to take it.
- VARUBI is taken on Day 1 of chemotherapy. Take 2 VARUBI tablets by mouth within 2 hours before you receive your anti-cancer medicine (chemotherapy).
- VARUBI can be taken with or without food.
- Do not take VARUBI more than 1 time every 14 days.
- If you take too much VARUBI, call your doctor or go to the nearest hospital emergency room right away.

What are the possible side effects of VARUBI?
VARUBI may cause serious side effects, including:

- Change in the level of some medicines in your blood. Serious or life-threatening reactions, including heart rhythm changes, may occur if VARUBI is used with certain other medicines. You should not take VARUBI if you take thioridazine or pimozide.

The most common side effects of VARUBI in people who take VARUBI and receive Cisplatin chemotherapy medicine include: low white blood cell count, hiccups, and stomach (abdominal) pain.
The most common side effects of VARUBI in people who take VARUBI and receive Anthracycline and Cyclophosphamide chemotherapy medicines include: decreased appetite, low white blood cell count, dizziness, indigestion, urinary tract infection, mouth sores, and low red blood cell count.
These are not all the possible side effects of VARUBI. Call your doctor for medical advice about side effects. You may report side effects to FDA at 1-800-FDA-1088.

How should I store VARUBI?

- VARUBI comes in a child-resistant package.
- Store VARUBI at room temperature between 68°F to 77°F (20°C to 25°C).

Keep VARUBI and all medicines out of the reach of children.

General information about the safe and effective use of VARUBI.
Medicines are sometimes prescribed for purposes other than those listed in a Patient Information leaflet. Do not use VARUBI for a condition for which it was not prescribed. Do not give VARUBI to other people, even if they have the same symptoms that you have. It may harm them. You can ask your doctor or pharmacist for information about VARUBI that is written for health professionals.

What are the ingredients in VARUBI?
Active ingredient: rolapitant
Inactive ingredients: colloidal silicon dioxide, croscarmellose sodium, lactose monohydrate, magnesium stearate, microcrystalline cellulose, povidone, and pregelatinized starch. The tablets are coated in non-functional blue and clear coats. The tablet coating comprises the following inactive ingredients: FD&C Blue No. 2-Indigo Carmine Lake, polyethylene glycol, polysorbate 80, polyvinyl alcohol, talc, and titanium dioxide.
Manufactured for: TerSera Therapeutics LLC, Deerfield, IL 60015
For more information, go to www.varubirx.com or call 1-844-334-4035.

This Patient Information has been approved by the U.S. Food and Drug Administration.

Revised: 8/2020

PACKAGE LABEL

PRINCIPAL DISPLAY PANEL - 90 mg Tablet Blister Wallet

NDC 70720-101-02

Single dose
180 mg total dose (2 x 90 mg tablets)

VARUBI®
(rolapitant) tablets

90 mg* per tablet

Contains two 90 mg tablets
equal to a single dose of 180 mg

*(equivalent to 100 mg rolapitant hydrochloride)

Rx only

For oral use.

Keep this and all drugs out of the reach of
children. This package is child-resistant.

Store at 20°C - 25°C (68°F - 77°F);
excursions permitted to 15°C - 30°C
(59°F - 86°F) [see USP Controlled
Room Temperature].

TerSera®
therapeutics

Manufactured for TerSera Therapeutics LLC
Deerfield, IL 60015

See package insert for dosage information.